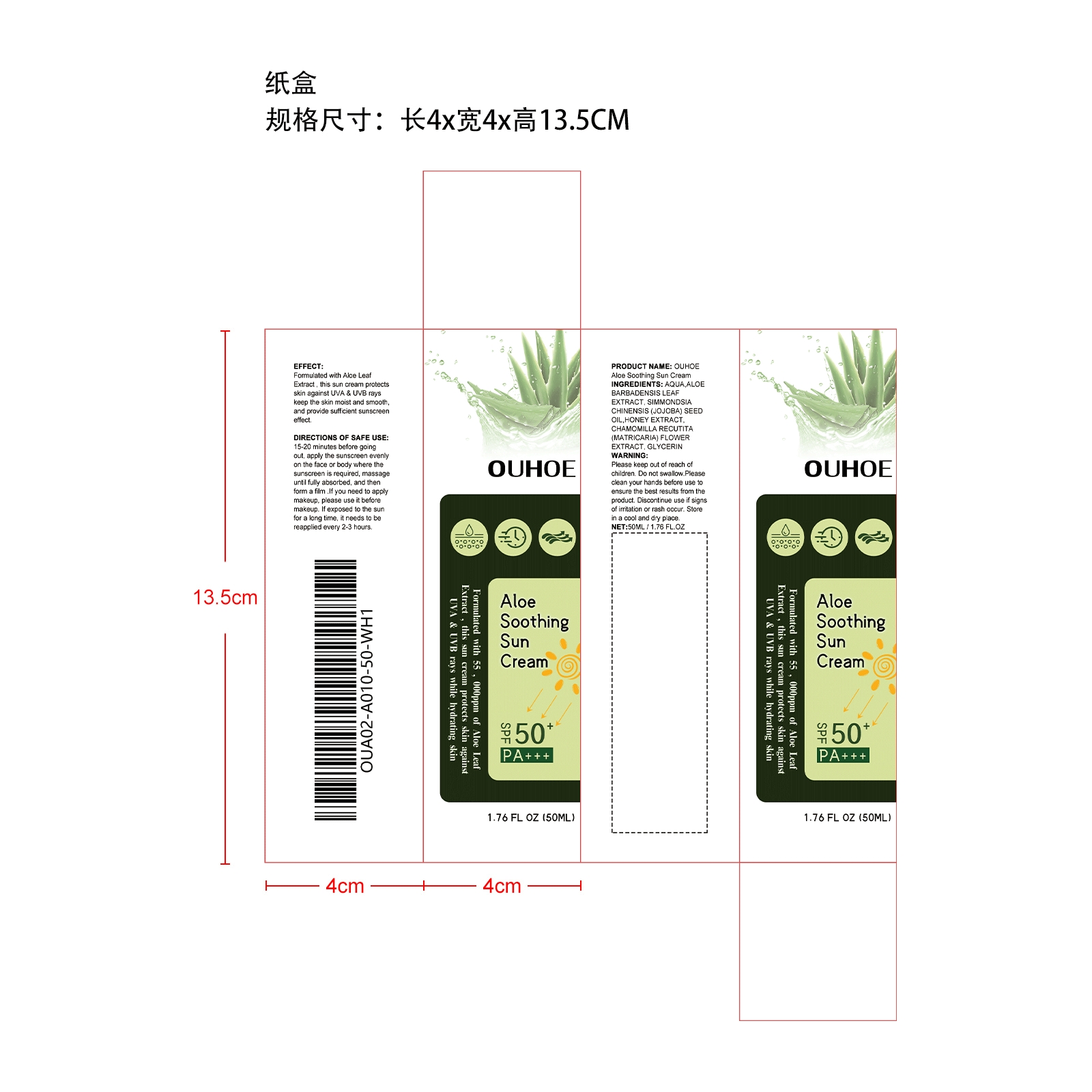 DRUG LABEL: OUHOE Aloe Soothing Sun Cream
NDC: 85163-003 | Form: CREAM
Manufacturer: Shantou Ouhoe Technology Co., Ltd.
Category: otc | Type: HUMAN OTC DRUG LABEL
Date: 20251127

ACTIVE INGREDIENTS: ALOE BARBADENSIS LEAF 0.05 mg/50 mg
INACTIVE INGREDIENTS: ETHYLHEXYL METHOXYCINNAMATE 2.5 mg/50 mg; OCTOCRYLENE 2.5 mg/50 mg; ISONONYL ISONONANOATE 2 mg/50 mg; GLYCERIN 0.75 mg/50 mg; AQUA 42.2 mg/50 mg

ACTIVE INGREDIENT

ALOE VERA LEAF

PURPOSE

Formulated with Aloe Leaf Extract , this sun cream protects skin against UVA & UVB rays keep the skin moist and smooth, and provide sufficient sunscreen effect.

WHEN USING

15-20 minutes before going out, apply the sunscreen evenly on the face or body where the sunscreen is required, massage until fully absorbed, and then form a film .If you need to apply makeup, please use it before makeup. If exposed to the sun for a long time, it needs to be reapplied every 2-3 hours.

DO NOT USE

Discontinue use if signs of irritation or rash occur.

STOP USE

Discontinue use if signs of irritation or rash occur.

KEEP OUT OF REACH OF CHILDREN

Please keep out of reach of children. Do not swallow.

WARNINGS

Please keep out of reach of children. Do not swallow.Please clean your hands before use to ensure the best results from the product. Discontinue use if signs of irritation or rash occur. Store in a cool and dry place.

STORAGE AND HANDLING

Store in a cool and dry place.

INACTIVE INGREDIENT

AQUA
ETHYLHEXYL METHOXYCINNAMATE
OCTOCRYLENE
ISONONYL ISONONANOATE
GLYCERIN